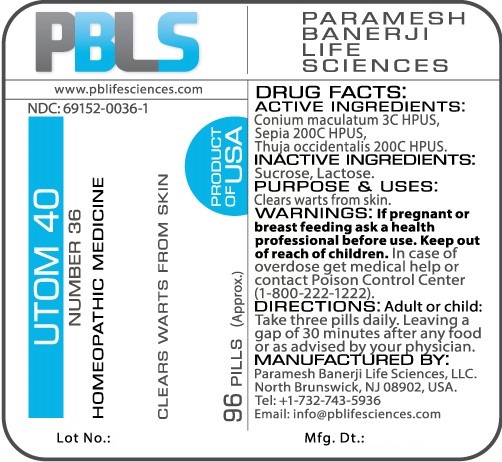 DRUG LABEL: Utom 40 Number 36
NDC: 69152-0036 | Form: PELLET
Manufacturer: Paramesh Banerji Life Sciences LLC
Category: homeopathic | Type: HUMAN OTC DRUG LABEL
Date: 20170215

ACTIVE INGREDIENTS: SEPIA OFFICINALIS JUICE 200 [hp_C]/1 1; CONIUM MACULATUM FLOWERING TOP 3 [hp_C]/1 1; THUJA OCCIDENTALIS LEAFY TWIG 200 [hp_C]/1 1
INACTIVE INGREDIENTS: SUCROSE; LACTOSE

DRUG FACTS: Active Ingredients

Conium Maculatum 3C HPUS, Sepia 200C HPUS, Thuja Occidentalis 200C HPUS

Inactive Ingredients

Sucrose, Lactose

Purpose

Clears warts on skin

Uses

Clears warts on skin

Warnings

If pregnant or breast feeding ask a health professional before use.

Keep out of reach of children. In case of overdose get medical help or contact a poison control center.

Direction

Adult or child: Take three pills daily. Leaving a gap of 30 minutes after any food or as advised by your physician.

Manufactured by

Paramesh Banerji Life Sciences, LLC.

North Brunswick, NJ 08902, USA.

Tel: +1-732-743-5936

Email: info@pblifesciences.com

Principal Display Panel

NDC: 69152-0036-1

Utom 40

Number 36

Homeopathic Medicine

Clears warts on skin

96 Pills (Approx.)

Product of USA